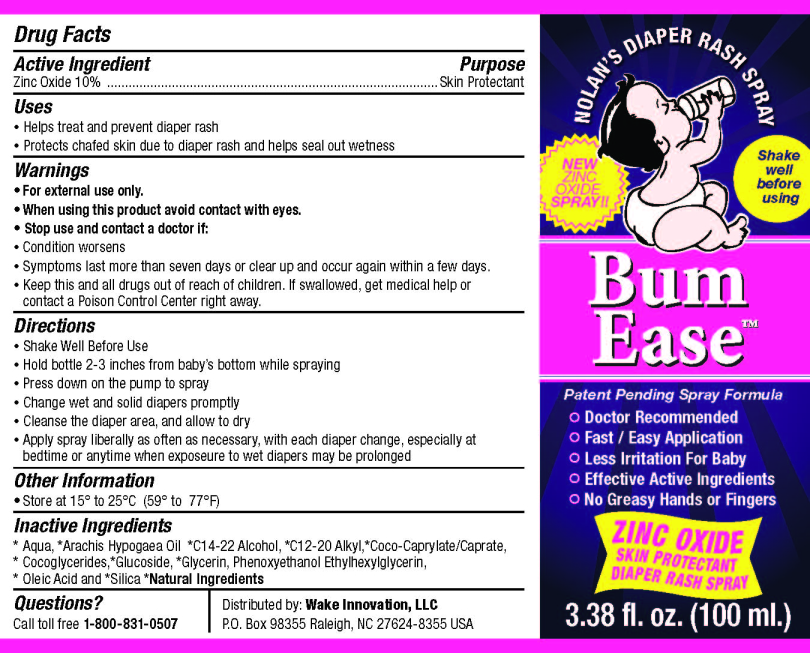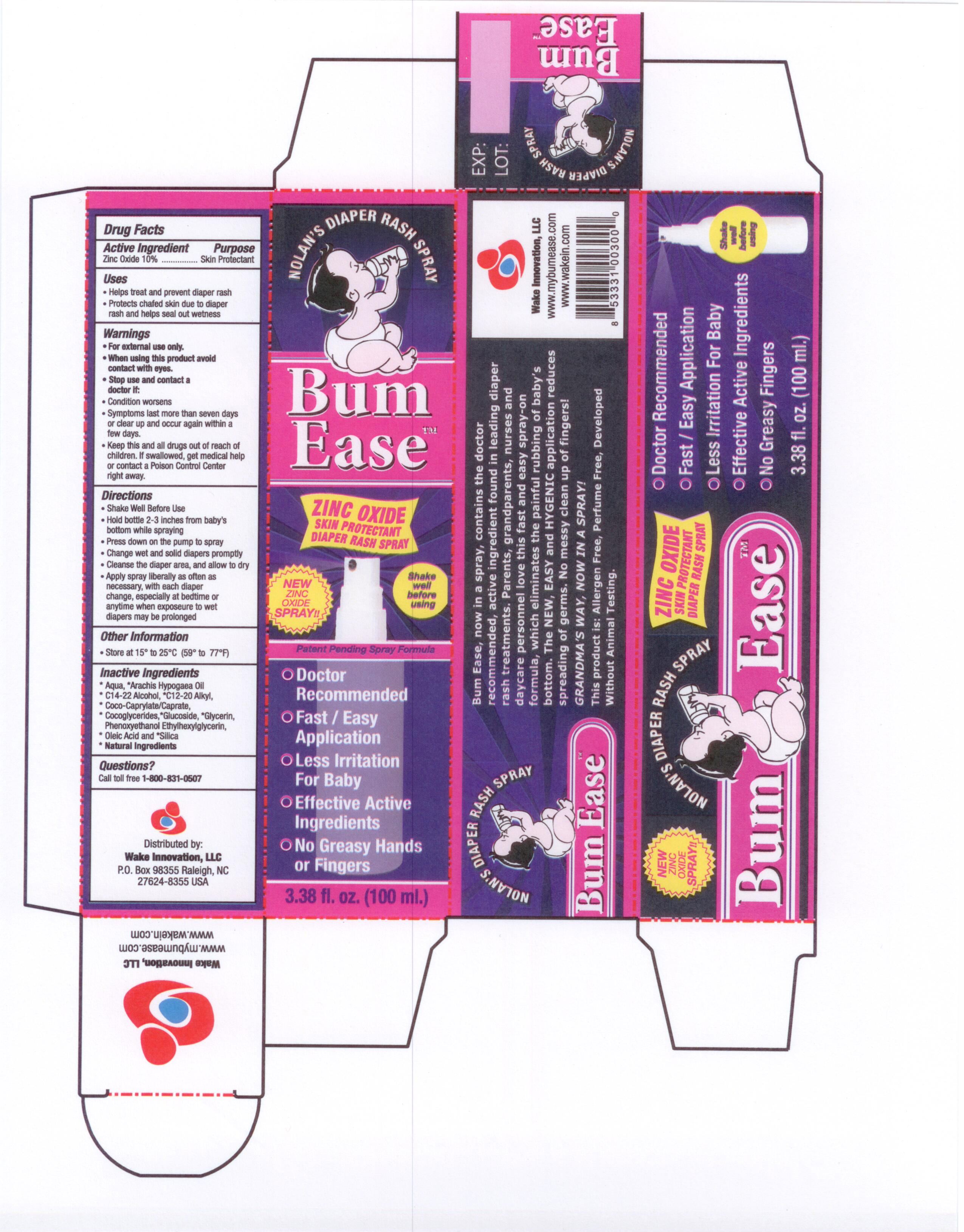 DRUG LABEL: Bum Ease
NDC: 76330-100 | Form: LIQUID
Manufacturer: Wake Innovation, LLC
Category: otc | Type: HUMAN OTC DRUG LABEL
Date: 20111205

ACTIVE INGREDIENTS: Zinc Oxide 10 g/100 mL
INACTIVE INGREDIENTS: Water; PEANUT OIL; COCONUT ACID; Glycerin; C14-22 ALCOHOLS; C12-20 Alkyl Glucoside; COCO-GLYCERIDES; Phenoxyethanol; Ethylhexylglycerin; Oleic Acid; SILICON DIOXIDE

Drug Facts

Active Ingredient

Zinc Oxide 10%

Purpose

Skin Protectant

Uses

• Helps treat and prevent diaper rash
• Protects chafed skin due to diaper rash and helps seal out wetness

Warnings

• For external use only.
• When using this product avoid contact with eyes.

Stop use and contact a doctor if:

• Condition worsens
• Symptoms last more than seven days or clear up and occur again within a few days.

KEEP OUT OF REACH OF CHILDREN

• Keep this and all drugs out of reach of children. If swallowed, get medical help or
contact a Poison Control Center right away.

Directions

• Shake Well Before Use
• Hold bottle 2-3 inches from baby’s bottom while spraying
• Press down on the pump to spray
• Change wet and solid diapers promptly
• Cleanse the diaper area, and allow to dry
• Apply spray liberally as often as necessary, with each diaper change, especially at
bedtime or anytime when exposeure to wet diapers may be prolonged

Other Information

• Store at 15° to 25°C (59° to 77°F)

Inactive Ingredients

*Aqua, *Arachis Hypogaea Oil *C14-22 Alcohol, *C12-20 Alkyl, *Coco-Caprylate/Caprate, *Cocoglycerides,
*Glucoside, *Glycerin, Phenoxyethanol Ethylhexylglycerin, *Oleic Acid and *Silica

*Natural Ingredients

Questions?

Call toll free 1-800-831-0507
Distributed by: Wake Innovation, LLC
P.O. Box 98355 Raleigh, NC
27624-8355 USA

Package Label

Nolan’s Diaper Rash Spray
Bum Ease ™
ZINC OXIDE SKIN PROTECTANT DIAPER RASH SPRAY
NEW ZINC OXIDE SPRAY!!
Shake well before using
Patent Pending Spray Formula
• Doctor Recommended
• Fast / Easy Application
• Less Irritation For Baby
• Effective Active Ingredients
• No Greasy Hands or Fingers
3.38 fl. oz. (100 ml.)